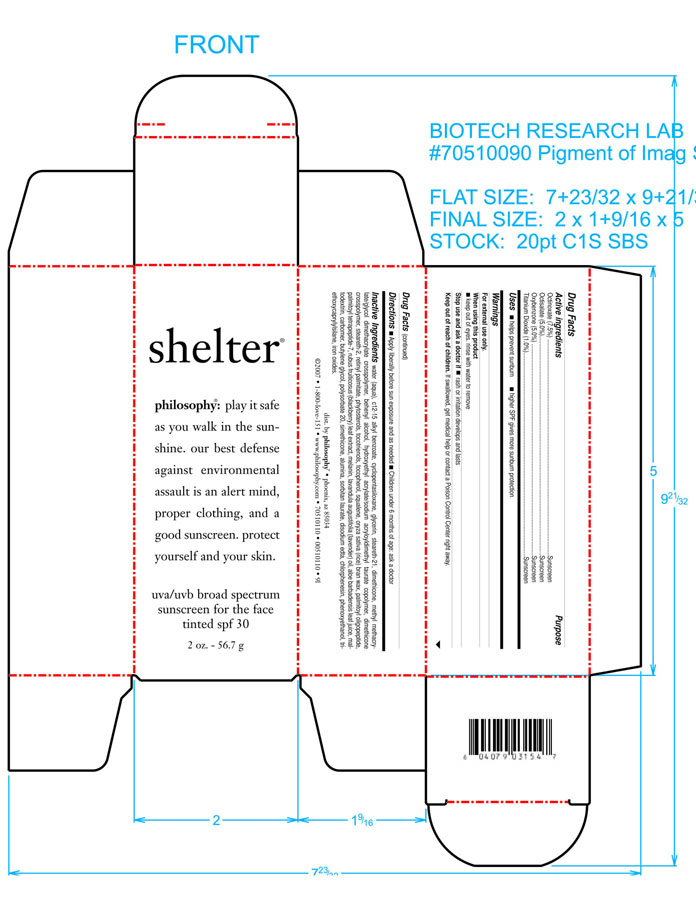 DRUG LABEL: Shelter 
NDC: 50184-4800 | Form: CREAM
Manufacturer: Philosophy, Inc.
Category: otc | Type: HUMAN OTC DRUG LABEL
Date: 20100223

ACTIVE INGREDIENTS: Octinoxate 75 mg/1 g; Octisalate 50 mg/1 g; Oxybenzone 50 mg/1 g; Titanium Dioxide 12 mg/1 g

Active Ingredients

ACTIVE INGREDIENT

Octinoxate......7.5%

Octisalate.......5.0%

Oxybenzone...... 5.0%

Titanium Dioxide......1.2%

Inactive Ingredients

water (aqua), c12-15 alkyl benzoate, cyclopentasiloxane, glycerin, steareth-21, dimethicone, methyl methacrylate/glycol dimethacrylate crosspolymer, behenyl alcohol, hydroxyethyl acrylate/sodium acryloyldimethyl taurate copolymer, dimethicone crosspolymer, steareth-2, retinyl palmitate, phytosterols, tocotrienols, tocopherol, squalene, oryza sative (rice) bran wax, palmitoyl oligopeptide, palmitoyl tetrapeptide-7, rubus fruticosus (blackberry) leaf extract, melanin, lavandula angustifolia (lavender) oil, aloe barbadensis leaf juice, maltodextrin, carbomer, butylene glycol, polysorbate 20, simethicone, alumina, sorbitan laurate, quercetin, diethylhexyl syringylidene malonate, capric caprylic triglycerides, disodium edta, chlorphenesin, phenoxyethanol.

Stop Use

STOP USE AND ASK A DOCTOR IF RASH OR IRRITATION DEVELOPS AND LASTS.

KEEP OUT OF REACH OF CHILDREN. IF SWALLOWED, GET MEDICAL HELP OR CONTACT A POISON CONTROL CENTER RIGHT AWAY.

WHEN USING

WHEN USING THIS PRODUCT KEEP OUT OF EYES. RINSE WITH WATER TO REMOVE.

INDICATIONS

HELPS PREVENT SUNBURN. HIGHER SPF GIVES MORE SUNBURN PROTECTION